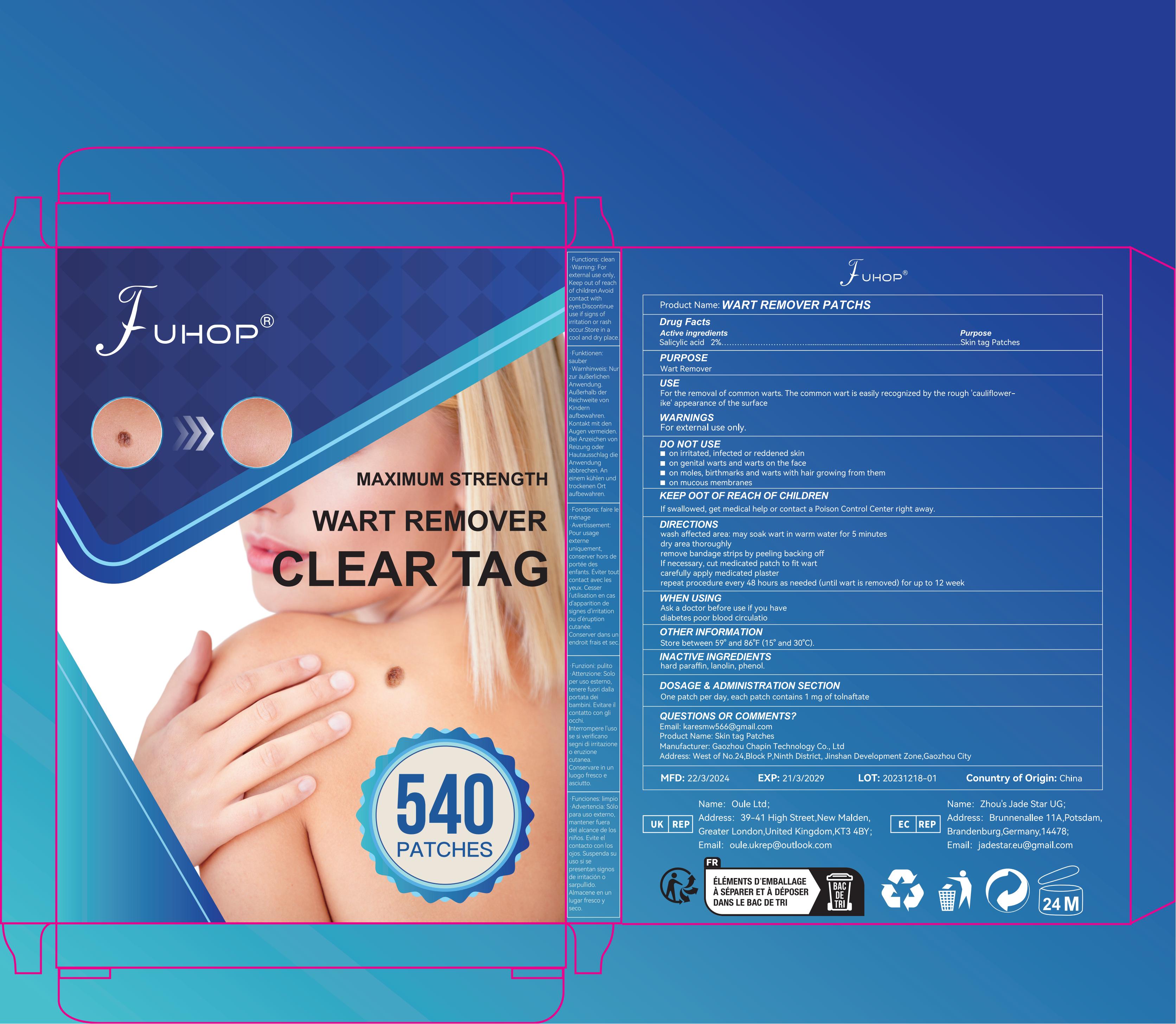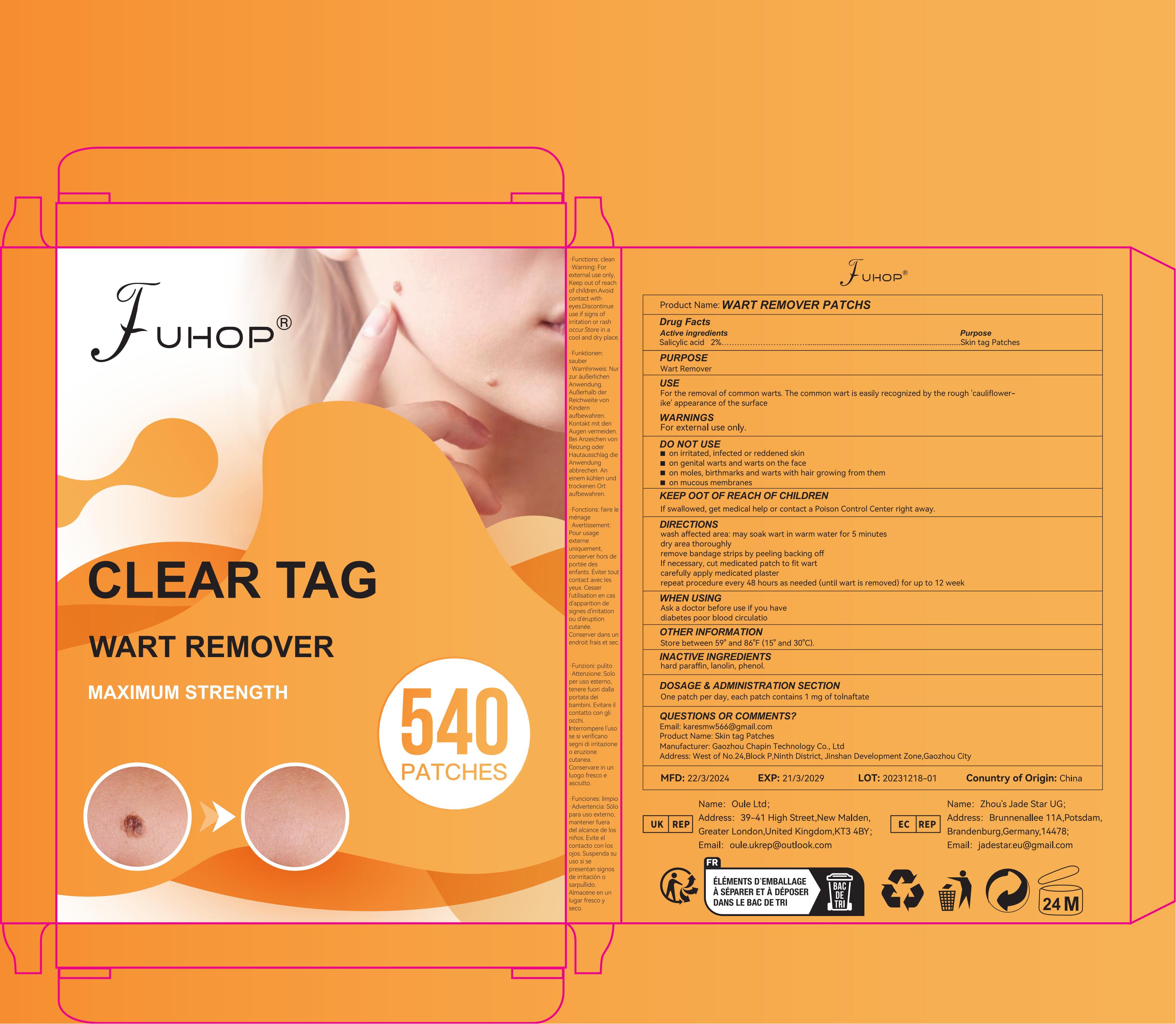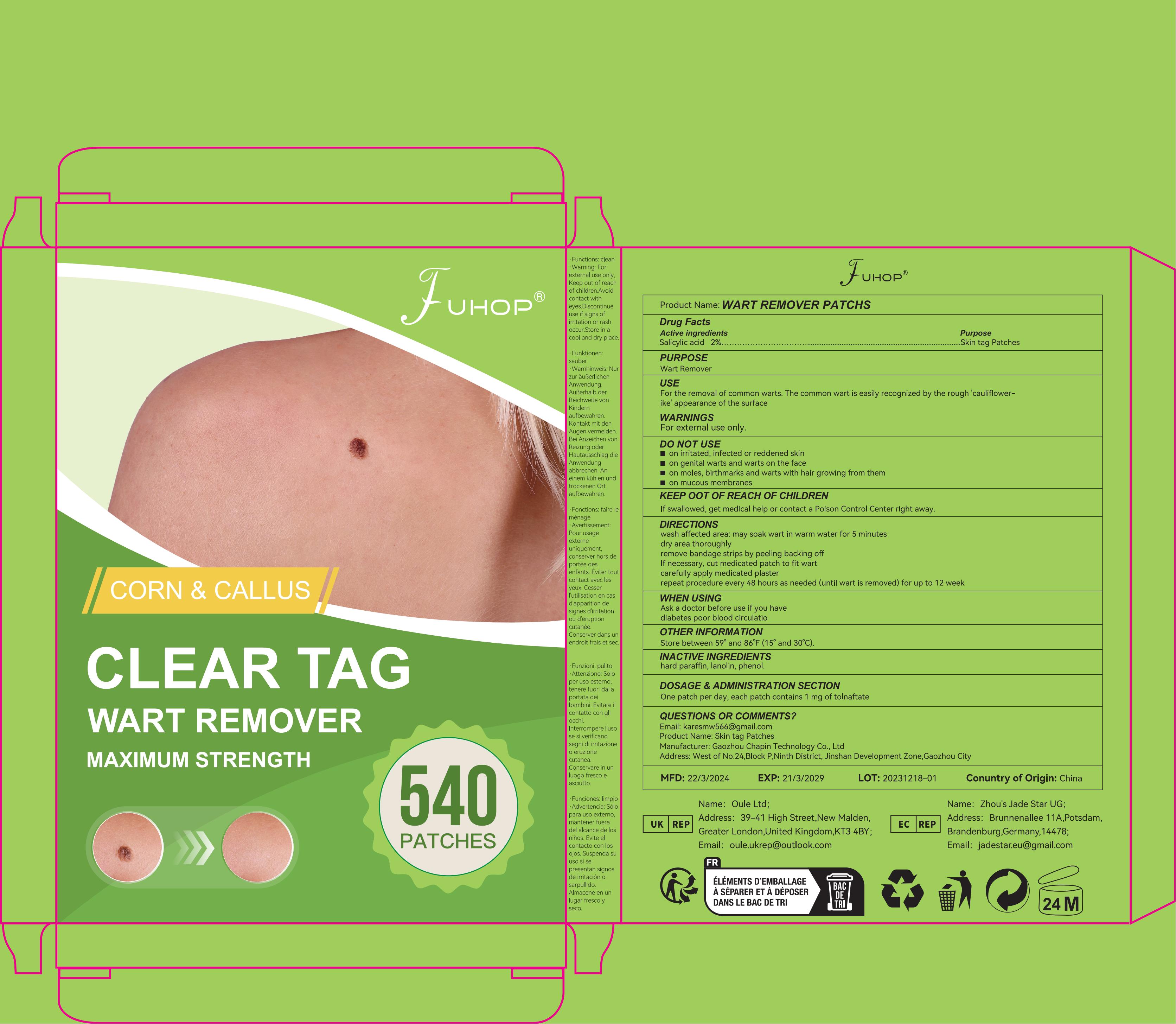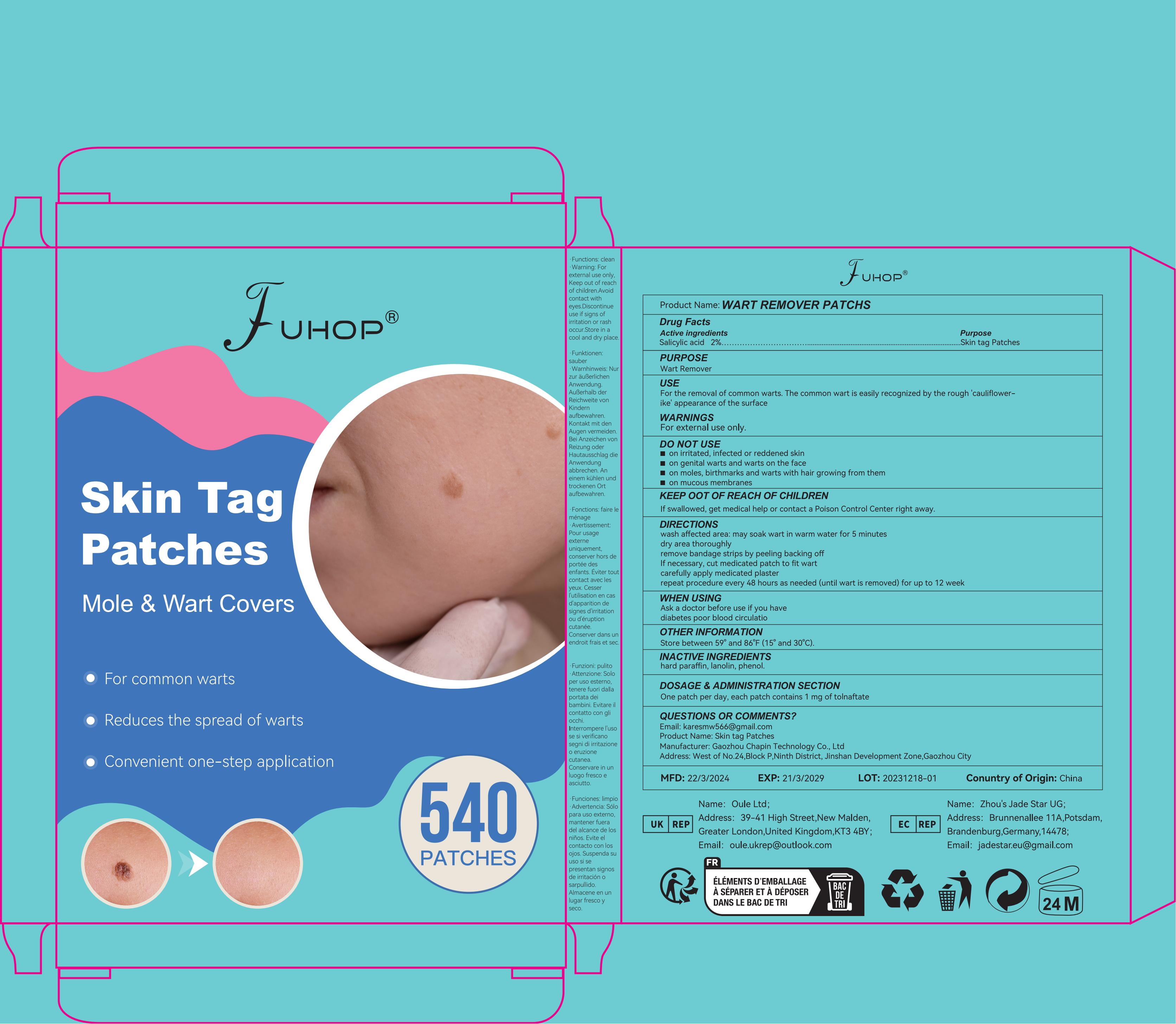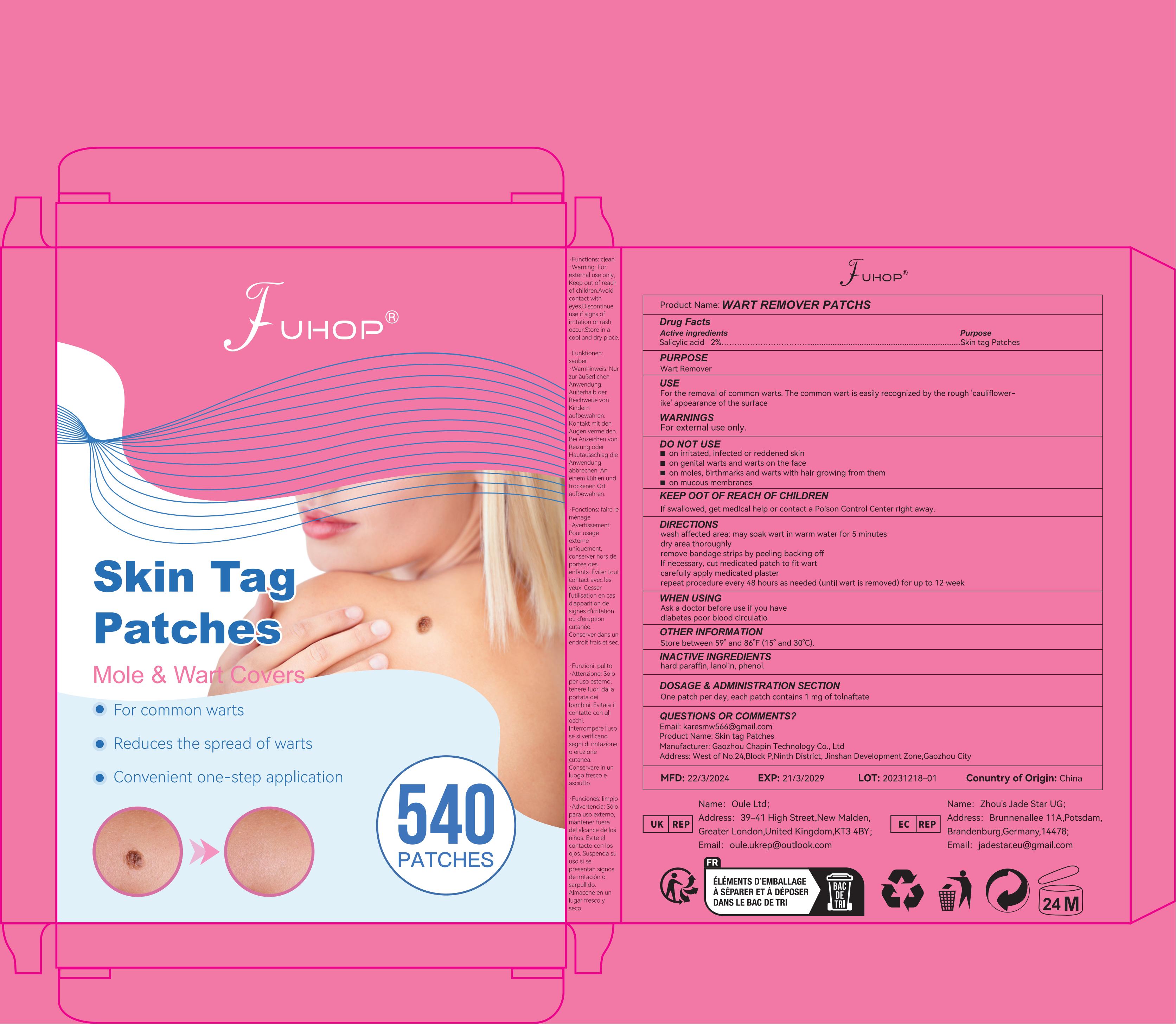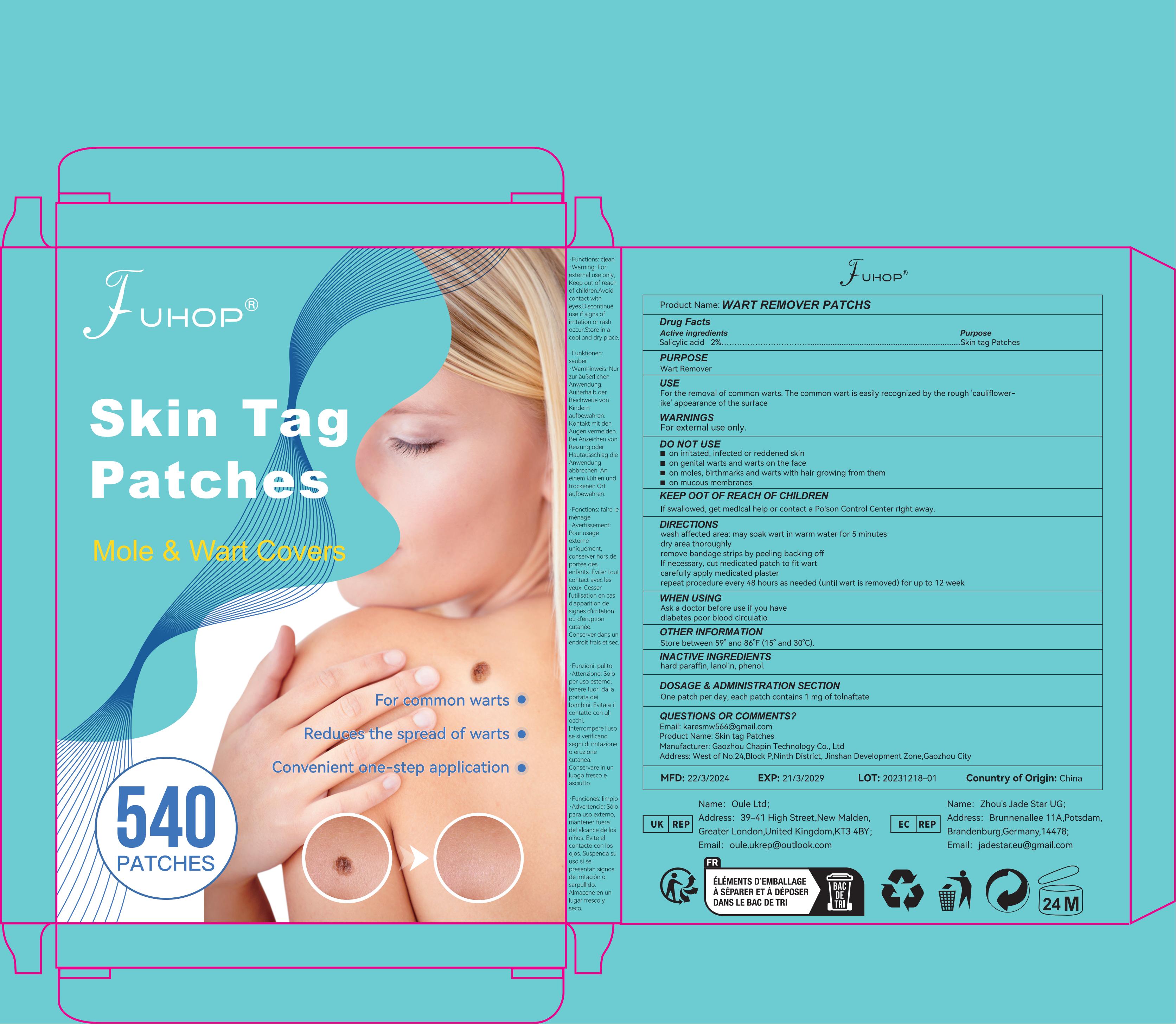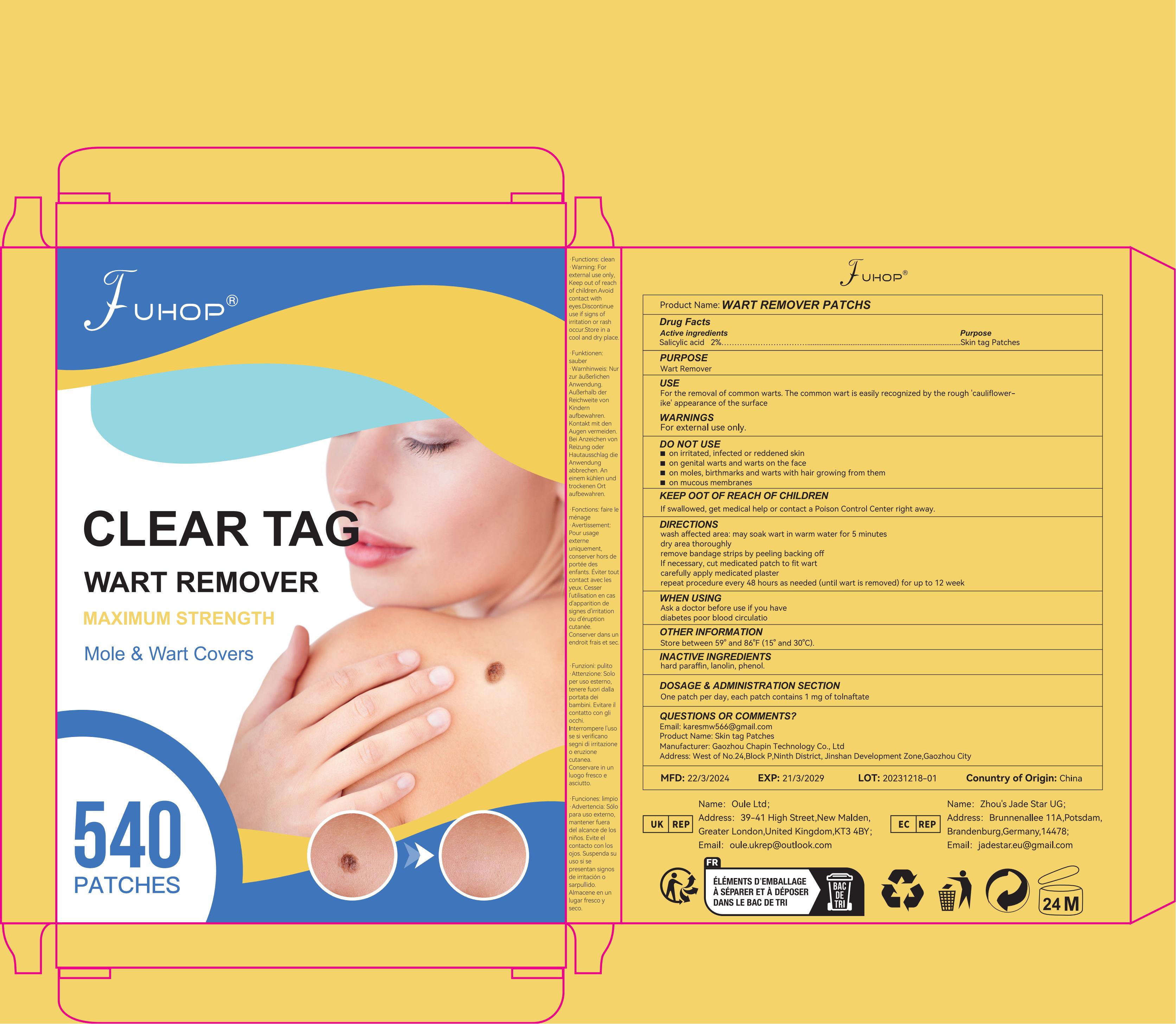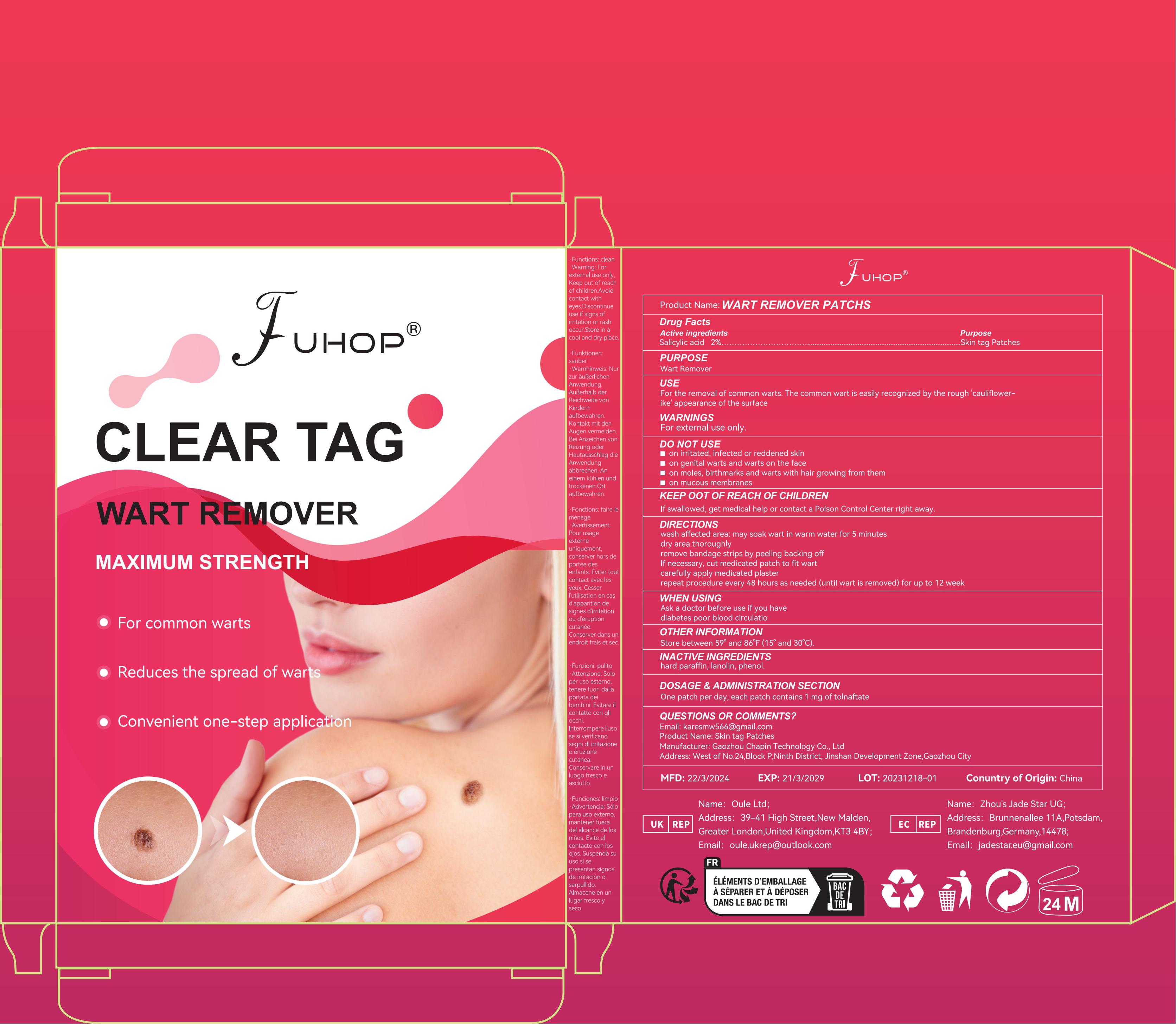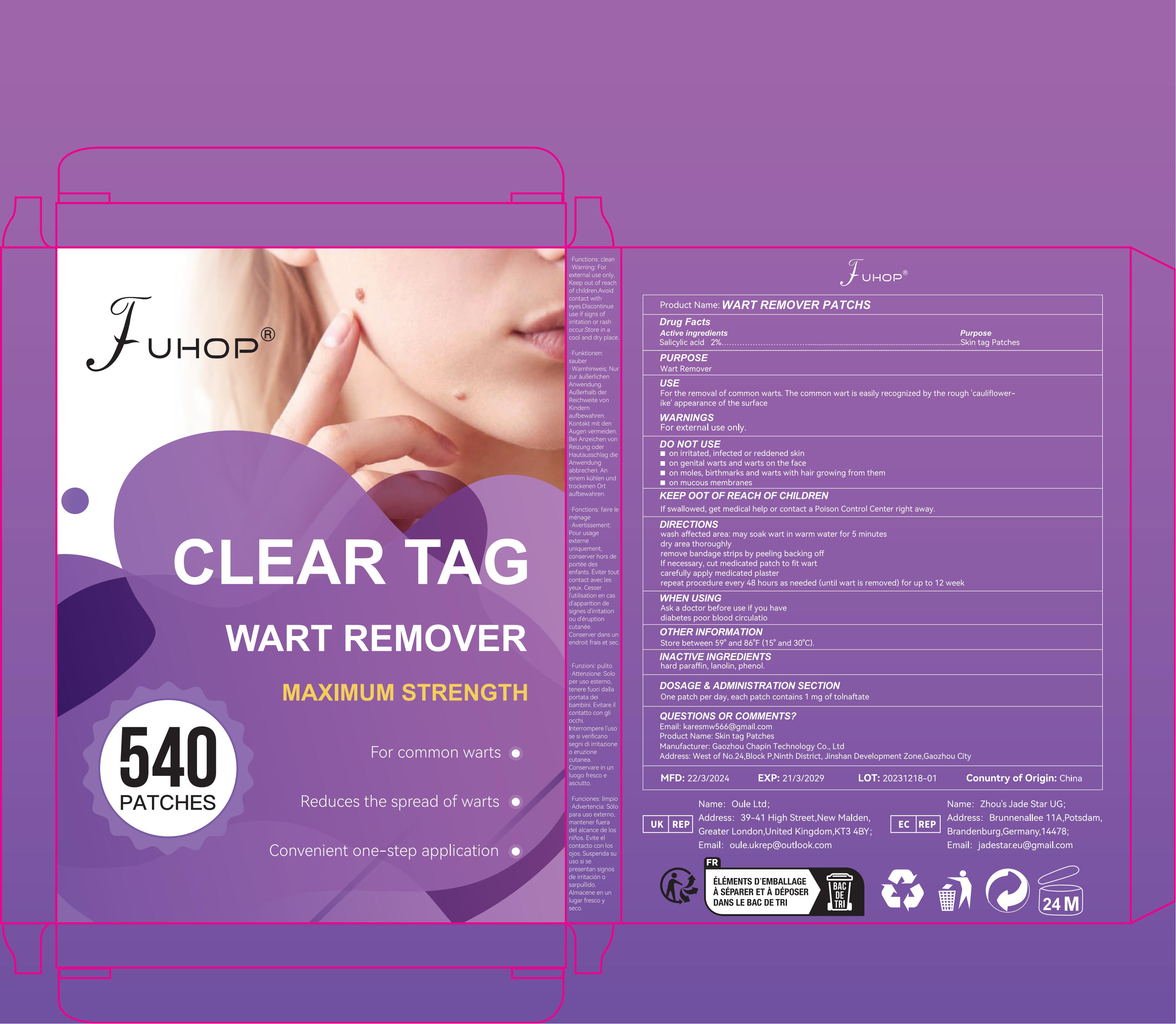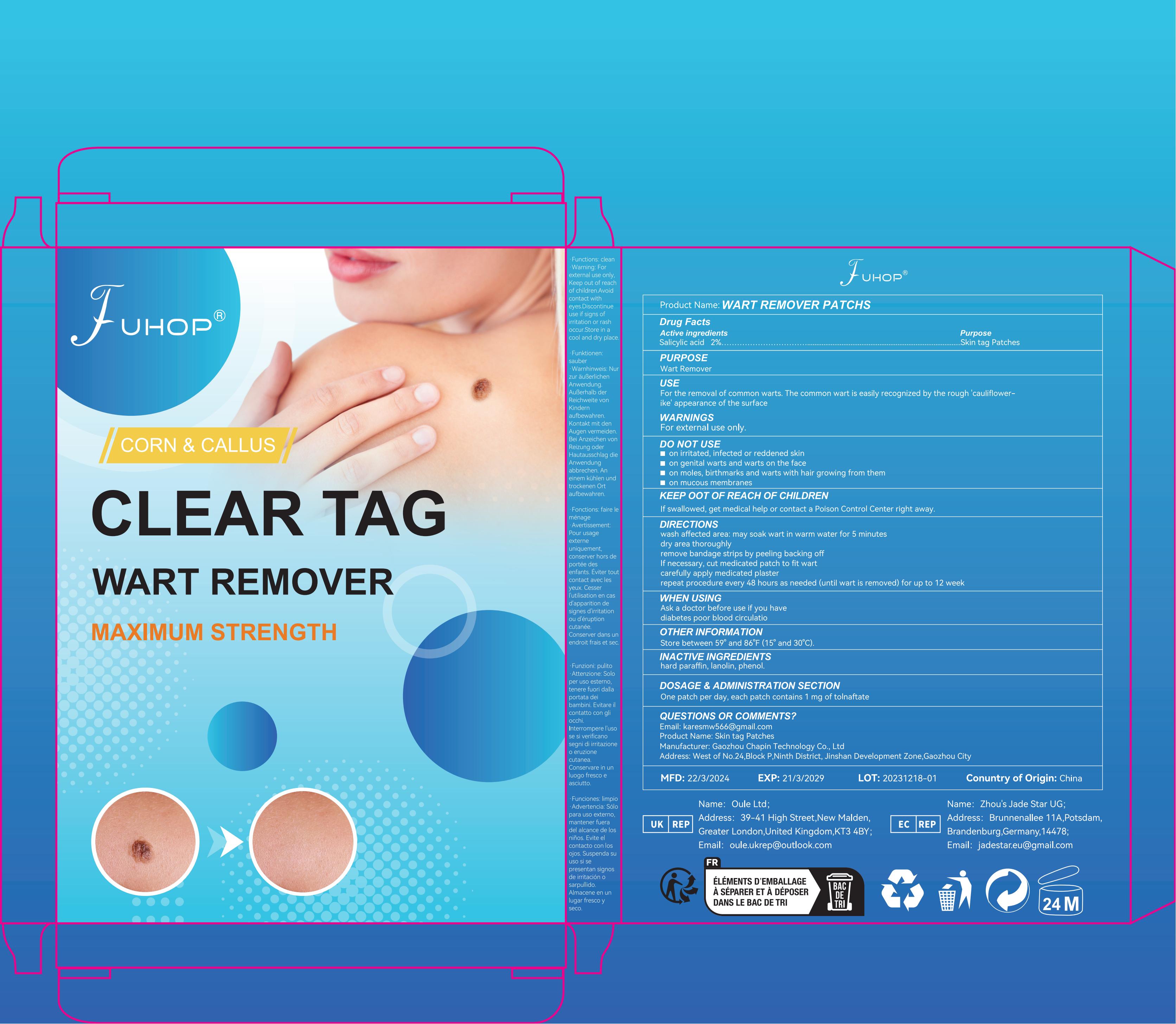 DRUG LABEL: WART REMOVER PATCHS
NDC: 84168-015 | Form: PATCH
Manufacturer: Gaozhou Chapin Technology Co., Ltd
Category: otc | Type: HUMAN OTC DRUG LABEL
Date: 20240625

ACTIVE INGREDIENTS: SALICYLIC ACID 200 mg/1 g
INACTIVE INGREDIENTS: ETHYLHEXYL ACRYLATE 380 mg/1 g; POLYETHYLENE TEREPHTHALATE (INTRINSIC VISCOSITY 0.40-0.70) 420 mg/1 g

ACTIVE INGREDIENT

Salicylic acid 20%

PURPOSE

Wart Remover

USE

For the removal of common warts. The common wart is easily recognized by the rough ‘cauliflower-like’ appearance of the surface.

WARNINGS

For external use only.

DO NOT USE

on irritated, infected or reddened skin
on genital warts and warts on the face
on moles, birthmarks and warts with hair growing from them
on mucous membranes

KEEP OUT OF REACH OF CHILDREN

If swallowed, get medical help or contact a Poison Control Center right away

DIRECTIONS

wash affected area: may soak wart in warm water for 5 minutes
dry area thoroughly
remove bandage strips by peeling backing off
If necessary, cut medicated patch to fit wart
carefully apply medicated plaster
repeat procedure every 48 hours as needed (until wart is removed) for up to 12 week

WHEN USING

Ask a doctor before use if you have
diabetes poor blood circulatio

OTHER INFORMATION

Store between 59° and 86°F (15° and 30°C).

INACTIVE INGREDIENTS

Ethylhexyl Acrylate ·Polyethylene Terephthalate

DOSAGE & ADMINISTRATION SECTION

One patch per day, each patch contains1 mg of tolnaftate